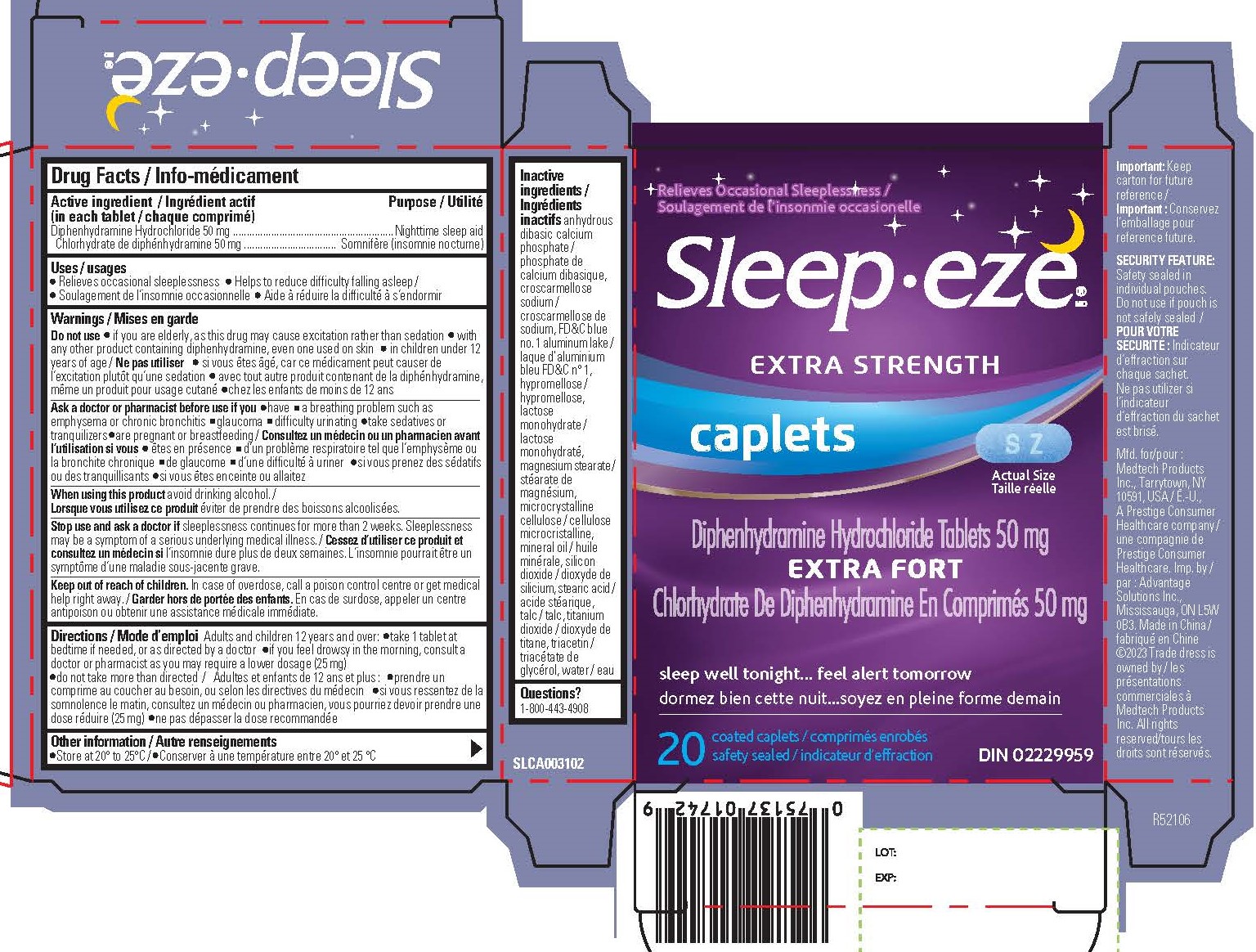 DRUG LABEL: Diphenhydramine Hydrochloride
NDC: 10267-4660 | Form: TABLET, FILM COATED
Manufacturer: Contract Pharmacal Corp.
Category: otc | Type: HUMAN OTC DRUG LABEL
Date: 20231130

ACTIVE INGREDIENTS: DIPHENHYDRAMINE HYDROCHLORIDE 50 mg/1 1
INACTIVE INGREDIENTS: CROSCARMELLOSE SODIUM; HYPROMELLOSES; LACTOSE MONOHYDRATE; STEARIC ACID; TRIACETIN; DIBASIC CALCIUM PHOSPHATE DIHYDRATE; MAGNESIUM STEARATE; MICROCRYSTALLINE CELLULOSE; LIGHT MINERAL OIL; SILICON DIOXIDE; TALC; TITANIUM DIOXIDE; FD&C BLUE NO. 1

4660- Export